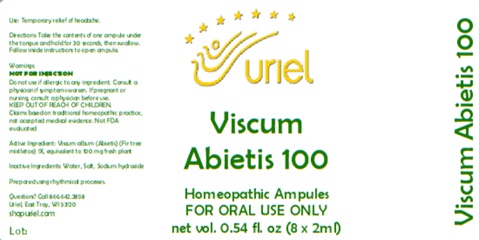 DRUG LABEL: Viscum Abietis 100
NDC: 48951-9307 | Form: LIQUID
Manufacturer: Uriel Pharmacy Inc.
Category: homeopathic | Type: HUMAN OTC DRUG LABEL
Date: 20251114

ACTIVE INGREDIENTS: VISCUM ALBUM FRUITING TOP 1 [hp_X]/1 mL
INACTIVE INGREDIENTS: SODIUM HYDROXIDE; WATER; SODIUM CHLORIDE

Viscum Abietis 100

PURPOSE

Use: Temporary relief of headache.

INDICATIONS AND USAGE

FOR ORAL USE ONLY

DOSAGE AND ADMINISTRATION

Take the contents of one ampule under the tongue and hold for 30 seconds, then swallow.

Warnings:
NOT FOR INJECTION
Do not use if allergic to any ingredient. Consult a physician if symptoms worsen. If pregnant or nursing, consult a physician before use.
Claims based on traditional homeopathic practice, not accepted medical evidence. Not FDA evaluated

KEEP OUT OF REACH OF CHILDREN.

Active Ingredient: Viscum album - Abietis (Fir tree mistletoe) 1X, equivalent to 100 mg fresh plant.

Inactive Ingredients: Water, Salt, Sodium hydroxide

Prepared using rhythmical processes.

QUESTIONS

Questions? Call 866.642.2858 Uriel, East Troy, WI 53120 shopuriel.com Lot: